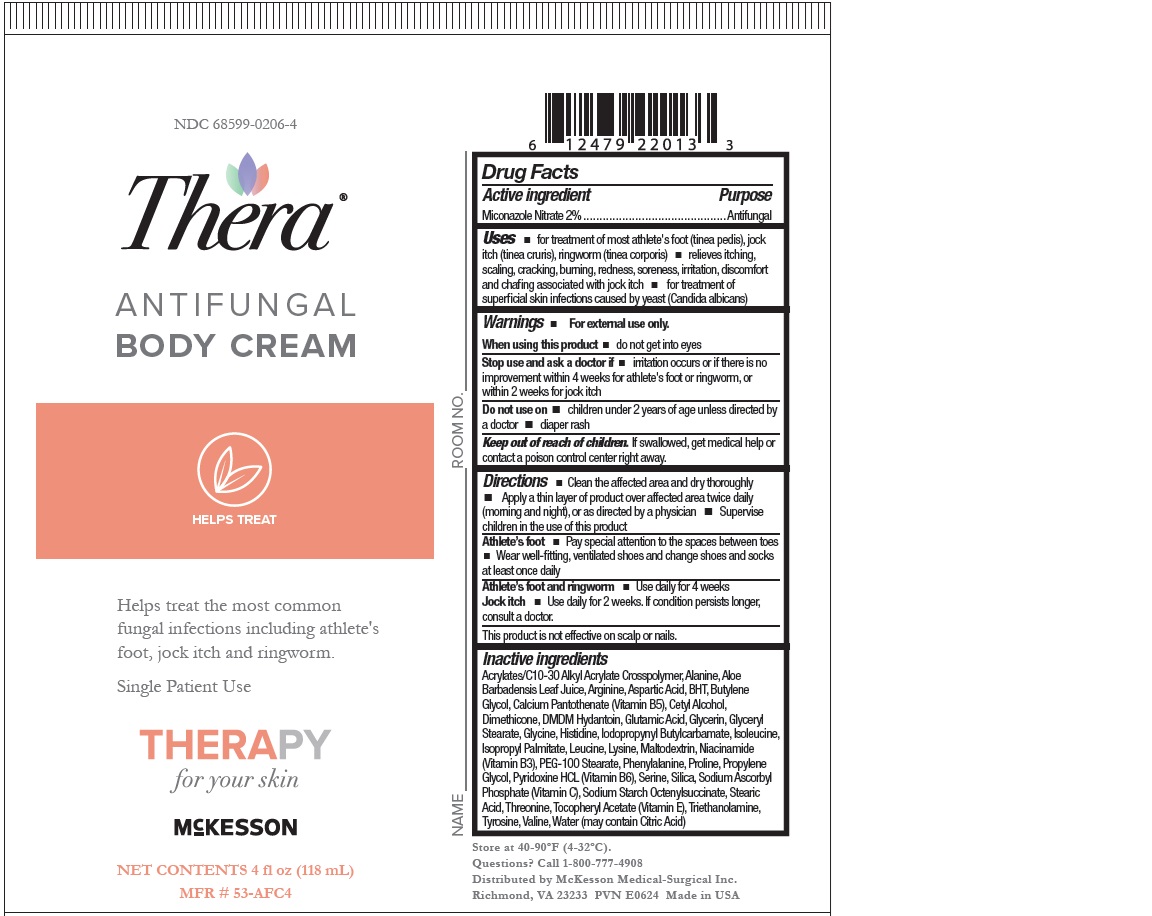 DRUG LABEL: Antifungal Body
NDC: 68599-0206 | Form: CREAM
Manufacturer: McKesson
Category: otc | Type: HUMAN OTC DRUG LABEL
Date: 20240613

ACTIVE INGREDIENTS: MICONAZOLE NITRATE 2 mg/100 mL
INACTIVE INGREDIENTS: 1-BUTENE; STEARIC ACID; CARBOMER INTERPOLYMER TYPE A (ALLYL SUCROSE CROSSLINKED); ALANINE; GLYCERIN; WATER; BUTYLATED HYDROXYTOLUENE; DIMETHICONE; ALOE; CALCIUM PANTOTHENATE; NIACINAMIDE; SILICON DIOXIDE; SODIUM ASCORBYL PHOSPHATE; ALUMINUM STARCH OCTENYLSUCCINATE; .ALPHA.-TOCOPHEROL ACETATE; LYSINE; ARGININE; THREONINE; PROLINE; GLYCINE; VALINE; PHENYLALANINE; DMDM HYDANTOIN; LEUCINE; TYROSINE; TROLAMINE; IODOPROPYNYL BUTYLCARBAMATE; ASPARTIC ACID; SERINE; MALTODEXTRIN; PYRIDOXINE HYDROCHLORIDE; HISTIDINE; GLUTAMIC ACID; GLYCERYL MONOSTEARATE; ISOPROPYL PALMITATE; PEG-100 STEARATE; ACRYLATES/C10-30 ALKYL ACRYLATE CROSSPOLYMER (60000 MPA.S); ETHYLENE GLYCOL; CETYL ALCOHOL

McKesson Antifungal Body Cream

Drug Facts

Active ingredient

Miconazole Nitrate 2%

Purpose

Antifungal

Uses

- for treatment of most athlete's foot (tinea pedis), jock itch (tinea cruris), ringworm (tinea corporis)
- relieves itching,scaling, cracking, burning, redness, soreness, irritation, discomfort and chafing associated with jock itch
- for treatment ofsuperficial skin infections caused by yeast (Candida albicans)

Warnings

- For External use only.

When using this product

- Do not get into eyes

Stop use and ask a doctor if

- irritation occurs or if there is no improvement within 4 weeks for athlete's foot or ringworm, or within 2 weeks for jock itch.

Do not use on

- children under 2 years of age unless directed by a doctor
- diaper rash

Keep out of reach of children.

If swallowed, get medical help or contact a poison control center right away.

Directions

- Clean the affected area and dry thoroughly
- Apply a thin layer of product over affected area twice daily (morning and night), or as directed by a physician
- Supervise children in the use of this product

Athlete’s foot

- Pay special attention to the spaces between toes
- Wear well-fitting, ventilated shoes and change shoes and socksat least once daily

Athlete’s foot and ringworm

- Use daily for 4 weeks

Jock itch

- Use daily for 2 weeks. If condition persists longer, consult a doctor.

This product is not effective on scalp or nails.

Inactive ingredients
Isopropyl Palmitate, Glyceryl Stearate, PEG 100 Stearate, Cyclopentasiloxane, Cetearyl Alcohol, Propylene Glycol, Polyquaternium-37, Propylene Glycol Dicaprylate/Dicaprate, PPG-1 Trideceth-6, Aloe Barbadensis Leaf Juice, Calcium Pantothenate (Vitamin B5), Maltodextrin, Niacinamide (Vitamin B3), Pyridoxine HCL (Vitamin B6), Silica, Sodium Ascorbyl Phosphate (Vitamin C), Sodium Starch Octenylsuccinate, Tocopherol Acetate (Vitamin E), Lysine, Histidine, Arginine, Aspartic Acid, Threonine, Serine, Glutamic Acid, Proline, Glycine, Alanine, Valine, Methionine, Isoleucine, Leucine, Tyrosine, Phenylalanine, Cysteine, Triethanolamine, DMDM Hydantoin, Iodopropynyl Butylcarbamate

PACKAGE LABEL

McKesson Thera Antifungal Body Cream

Helps treat the most common fungal infections including athlete's foot, jock itch and ringworm.

Single Patient Use

Therapy [for the skin]

Net Contents 4 fl oz (118ml)

MFR# 53-AFC4